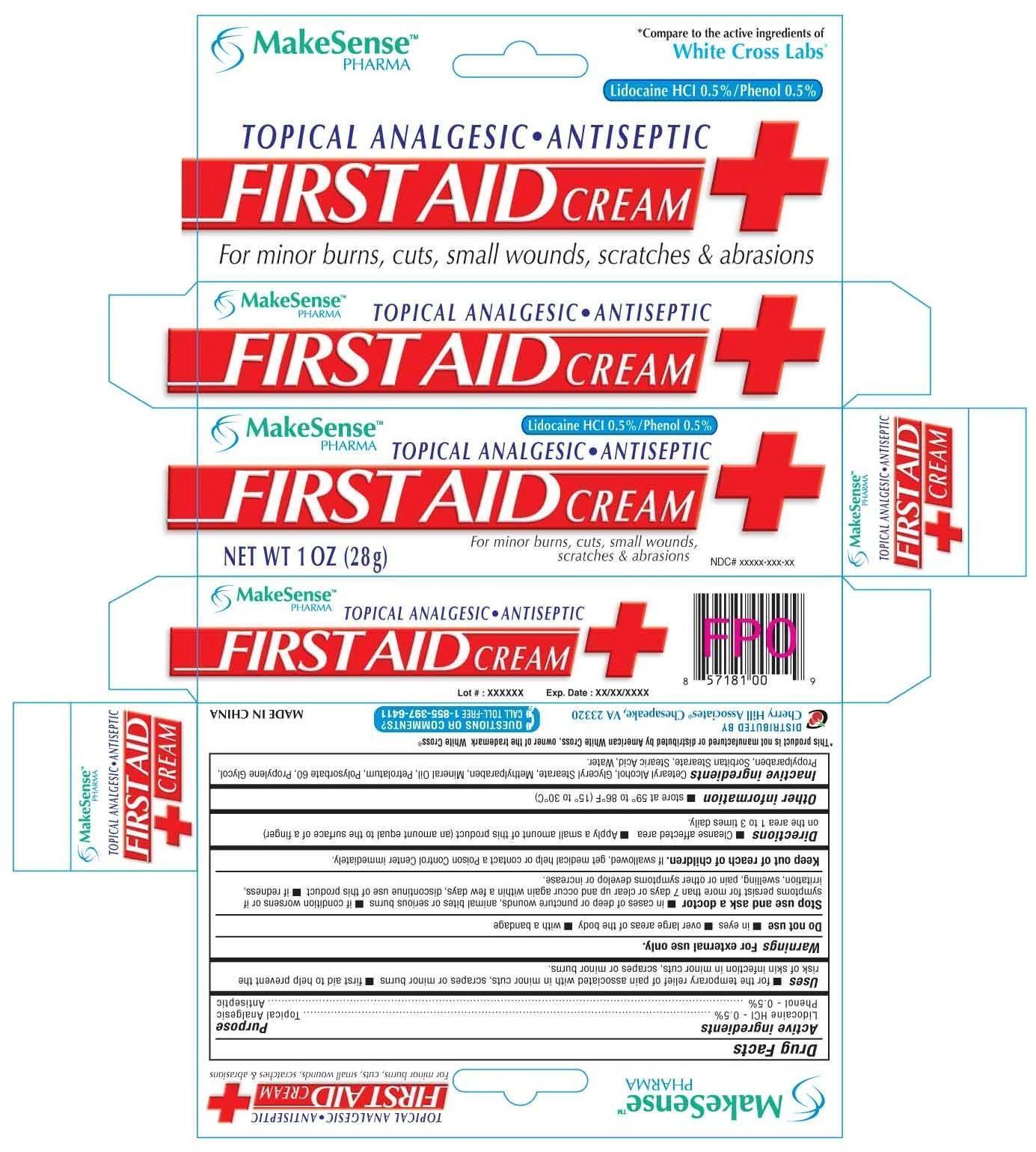 DRUG LABEL: MAKESENSE
NDC: 69020-210 | Form: CREAM
Manufacturer: Cherry Hill Sales Co
Category: otc | Type: HUMAN OTC DRUG LABEL
Date: 20140807

ACTIVE INGREDIENTS: LIDOCAINE HYDROCHLORIDE ANHYDROUS 0.5 g/100 g; PHENOL 0.5 g/100 g
INACTIVE INGREDIENTS: CETOSTEARYL ALCOHOL; GLYCERYL STEARATE SE; METHYLPARABEN; MINERAL OIL; PETROLATUM; POLYSORBATE 20; PROPYLPARABEN; SORBITAN MONOSTEARATE; STEARIC ACID; WATER

Drug Facts

Active ingredients

Lidocaine HCl 0.5%

Phenol 0.5%

Purpose

Topical Analgesic

Antiseptic

Uses

■ for the temporary relief of pain associated with minor cuts, scrapes or minor burns ■ first aid to help prevent the risk of skin infection in minor cuts, scrapes or minor burns

Warnings

For external use only

Do not use

■ in eyes ■ over large areas of the body ■ with a bandage

Stop use and consult a doctor if

■ in cases of deep or puncture wounds, animal bites or serious burns ■ if condition worsens or if symptoms persist for more than 7 days or clear up and occur again within a few days, discontinue use of this product ■ if redness, irritation, swelling, pain or other symptoms develop or increase

Keep out of reach of children

If swallowed, get medical help or contact a Poison Control Center right away.

Directions

■ Cleanse affected area ■ Apply a small amount of this product (an amount equal to the surface of a finger) on the area 1 to 3 times daily

Other Information

■ store at room temperature 59 to 86F (15 to 30C) ■ see carton or tube crimp for lot number and expiration date

Inactive ingredients

Cetearyl Alcohol, Glyceryl Stearate, Methylparaben, Mineral Oil, Petrolatum, Polysorbate 60, Propylene Glycol, Propylparaben, Purified Water, Sorbitan Stearate, Stearic Acid